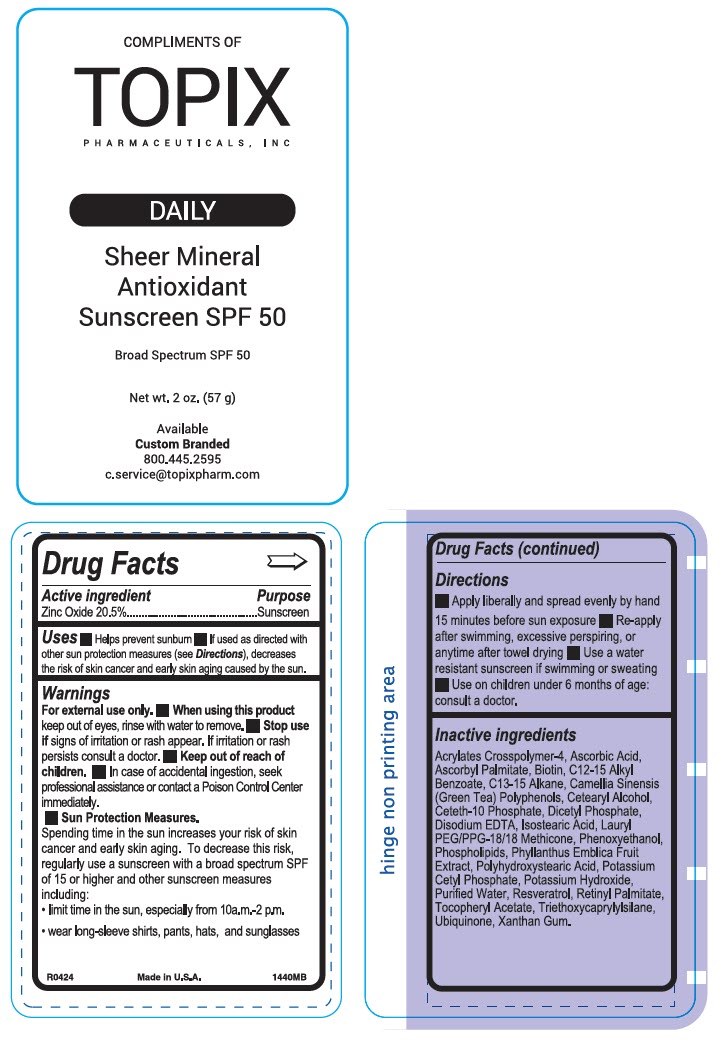 DRUG LABEL: Sheer Mineral Antioxidant Sunscreen
NDC: 51326-144 | Form: LOTION
Manufacturer: Topiderm, Inc.
Category: otc | Type: HUMAN OTC DRUG LABEL
Date: 20250307

ACTIVE INGREDIENTS: ZINC OXIDE 205 mg/1 g
INACTIVE INGREDIENTS: ACRYLATES CROSSPOLYMER-4; ASCORBIC ACID; ASCORBYL PALMITATE; BIOTIN; ALKYL (C12-15) BENZOATE; C13-15 ALKANE; GREEN TEA LEAF; CETOSTEARYL ALCOHOL; CETETH-10 PHOSPHATE; DIHEXADECYL PHOSPHATE; EDETATE DISODIUM; ISOSTEARIC ACID; LAURYL PEG/PPG-18/18 METHICONE; PHENOXYETHANOL; HYDROGENATED SOYBEAN LECITHIN; PHYLLANTHUS EMBLICA FRUIT; POLYHYDROXYSTEARIC ACID (2300 MW); POTASSIUM CETYL PHOSPHATE; POTASSIUM HYDROXIDE; WATER; RESVERATROL; VITAMIN A PALMITATE; .ALPHA.-TOCOPHEROL ACETATE; TRIETHOXYCAPRYLYLSILANE; UBIDECARENONE; XANTHAN GUM

Sheer Mineral Antioxidant Sunscreen
SPF50

Drug Facts

Active ingredient

Zinc Oxide 20.5%

Purpose

Sunscreen

Uses

- Helps prevent sunburn
- If used as directed with other sun protection measures (see Directions), decreases the risk of skin cancer and early skin aging caused by the sun.

Warnings

For external use only.

- When using this product keep out of eyes, rinse with water to remove.

- Stop use if signs of irritation or rash appear. If irritation or rash persists consult a doctor.

- Keep out of reach of children.
- In case of accidental ingestion, seek professional assistance or contact a Poison Control Center immediately.

- Sun Protection Measures.

Spending time in the sun increases your risk of skin cancer and early skin aging. To decrease this risk, regularly use a sunscreen with a broad spectrum SPF of 15 or higher and other sunscreen measures including:

- limit time in the sun, especially from 10a.m.-2 p.m.
- wear long-sleeve shirts, pants, hats, and sunglasses

Directions

- Apply liberally and spread evenly by hand 15 minutes before sun exposure
- Re-apply after swimming, excessive perspiring, or anytime after towel drying
- Use a water resistant sunscreen if swimming or sweating
- Use on children under 6 months of age: consult a doctor.

Inactive ingredients

Acrylates Crosspolymer-4, Ascorbic Acid, Ascorbyl Palmitate, Biotin, C12-15 Alkyl Benzoate, C13-15 Alkane, Camellia Sinensis (Green Tea) Polyphenols, Cetearyl Alcohol, Ceteth-10 Phosphate, Dicetyl Phosphate, Disodium EDTA, Isostearic Acid, Lauryl PEG/PPG-18/18 Methicone, Phenoxyethanol, Phospholipids, Phyllanthus Emblica Fruit Extract, Polyhydroxystearic Acid, Potassium Cetyl Phosphate, Potassium Hydroxide, Purified Water, Resveratrol, Retinyl Palmitate, Tocopheryl Acetate, Triethoxycaprylylsilane, Ubiquinone, Xanthan Gum.

PRINCIPAL DISPLAY PANEL - 57 g Container Label

COMPLIMENTS OF

TOPIX
PHARMACEUTICALS, INC

DAILY

Sheer Mineral
Antioxidant
Sunscreen SPF 50

Broad Spectrum SPF 50

Net wt. 2 oz. (57 g)

Available
Custom Branded
800.445.2595
c.service@topixpharm.com